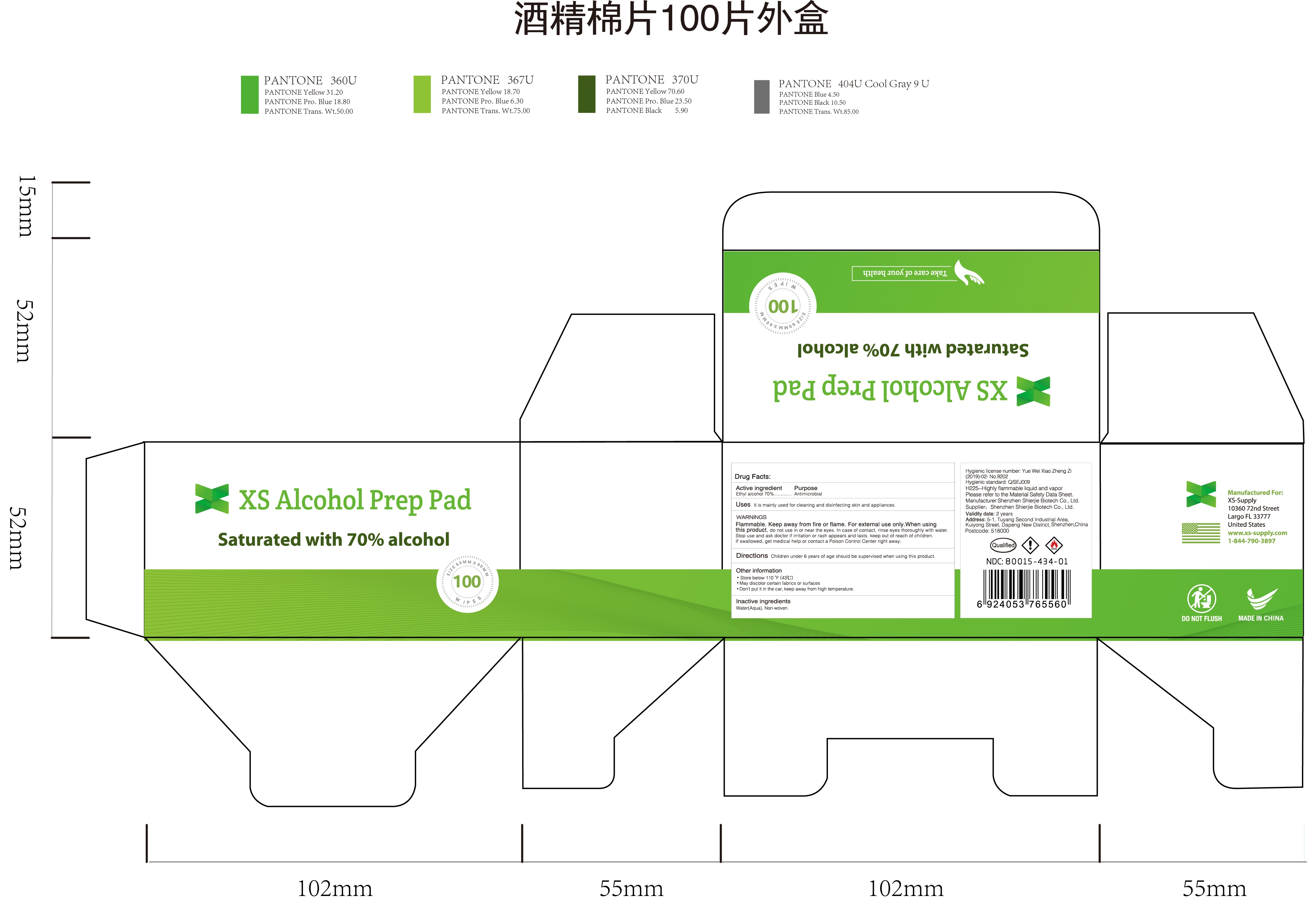 DRUG LABEL: XS Alcohol Prep Pad Saturated with 70% alcohol
NDC: 43116-022 | Form: CLOTH
Manufacturer: Shenzhen Shierjie Biological Engineering Co., LTD
Category: otc | Type: HUMAN OTC DRUG LABEL
Date: 20201122

ACTIVE INGREDIENTS: ALCOHOL 70 mL/100 1
INACTIVE INGREDIENTS: WATER

43116-022
XS Alcohol Prep Pad Saturated with 70% alcohol

Active Ingredient

alcohol70%

Purpose

Antimicrobial

Uses

It is mainly used for cleaning and disinfecting skin and appliances

Warnings

Flammable. Keep away from fire or flame For external use only.

When using this product, do not use in or near the eyes. In case of contact, rinse eyes thoroughly with water

Stop use and ask doctor if irritation or rash appears and lasts.

keep out of reach of children. If swallowed, get medical help or contact a Poison Control Center right away

When using this product, do not use in or near the eyes. In case of contact, rinse eyes thoroughly with water

When using this product, do not use in or near the eyes. In case of contact, rinse eyes thoroughly with water

Stop use and ask doctor if irritation or rash appears and lasts.

keep out of reach of children. If swallowed, get medical help or contact a Poison Control Center right away

Stop use and ask doctor if irritation or rash appears and lasts.

keep out of reach of children. If swallowed, get medical help or contact a Poison Control Center right away

Directions

Children under 6 years of age should be supervised when using this product

Other information

Store below110°F(43℃)
May discolor certain fabrics or surfaces
Don 't put it in the car, keep away from high temperature

Inactive ingredients

Water(Aqua), Non-woven